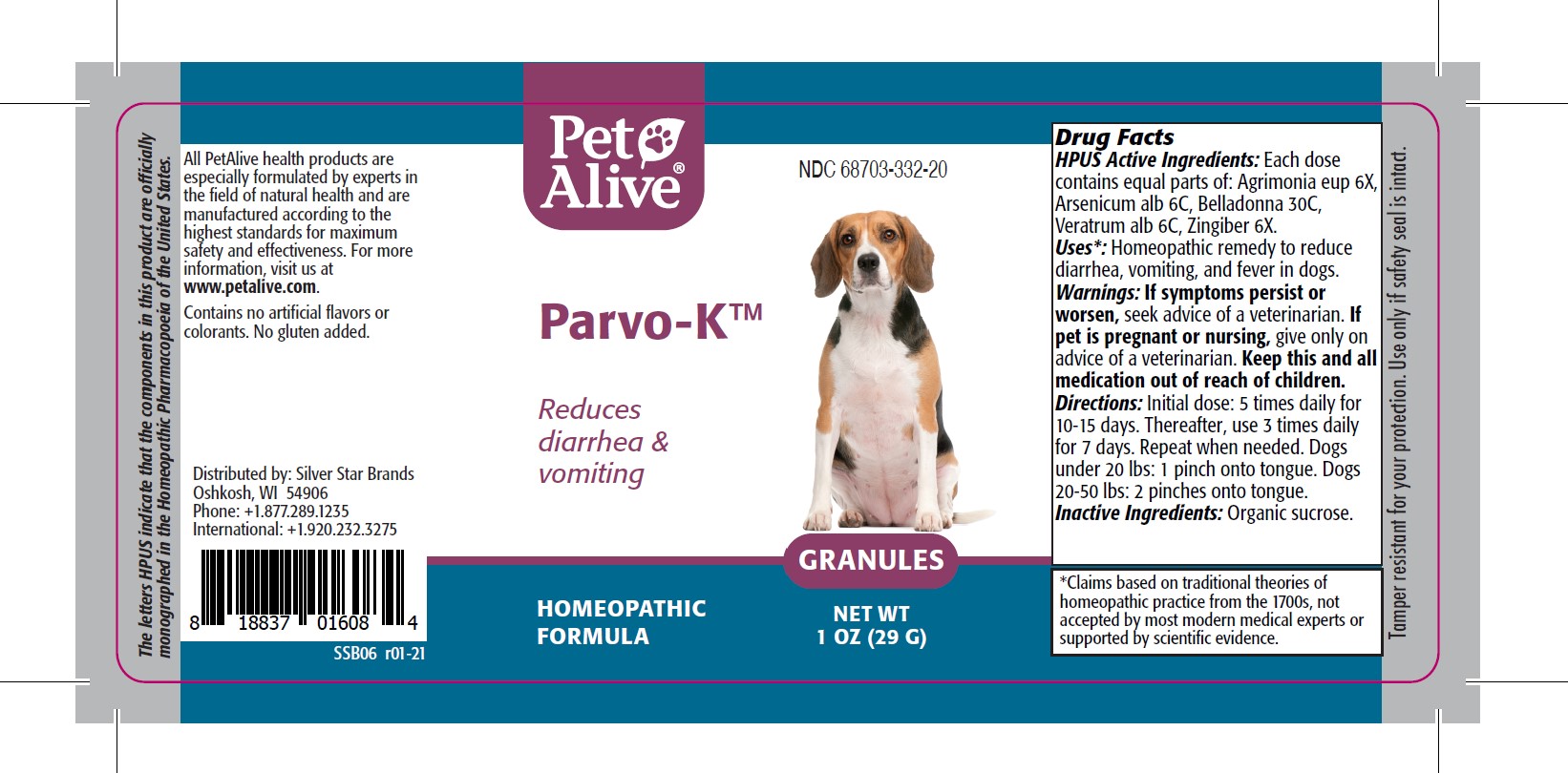 DRUG LABEL: PetAlive Parvo-K
NDC: 68703-332 | Form: GRANULE
Manufacturer: SILVER STAR BRANDS
Category: homeopathic | Type: OTC ANIMAL DRUG LABEL
Date: 20251216

ACTIVE INGREDIENTS: AGRIMONIA EUPATORIA 6 [hp_X]/16 mg; ARSENIC TRIOXIDE 6 [hp_C]/16 mg; ATROPA BELLADONNA 30 [hp_C]/16 mg; VERATRUM ALBUM ROOT 6 [hp_C]/16 mg; GINGER 6 [hp_X]/16 mg
INACTIVE INGREDIENTS: SUCROSE

PetAlive Parvo-K

PURPOSE

Reduces diarrhea and vomiting

HPUS Active Ingredients:

Agrimonia eup 6X
Arsenicum alb 6C
Belladonna 30C
Veratrum alb 6C
Zingiber 6X

INDICATIONS AND USAGE

Uses: Homeopathic remedy to reduce diarrhea, vomiting, and fever in dogs

WARNINGS

Warnings: If symptoms persist or worsen, seek advice of a veterinarian

PREGNANCY OR BREAST FEEDING

If pet is pregnant or nursing, give only on advice of a veterinarian.

KEEP OUT OF REACH OF CHILDREN

Keep this and all medication out of reach of children.

DOSAGE AND ADMINISTRATION

Directions: Initial dose: 5 times daily for 10-15 days. Thereafter, use 3 times daily for 7 days. Repeat when needed. Dogs under 20 lbs: 1 pinch onto tongue. Dogs 20-50 lbs: 2 pinches onto tongue.

Inactive Ingredients: Organic sucrose

INFORMATION FOR OWNERS/CAREGIVERS

The letters HPUS indicate that the components in this product are officially monographed in the Homeopathic Pharmacopoeia of the United States.

All PetAlive health products are especially formulated by experts in the field of natural health and are manufactured according to the highest standards for maximum safety and effectiveness. For more information, visit us at www.petalive.com.

Contains no artificial flavors or colorants. No gluten added.

Distributed by: Silver Star Brands
Oshkosh, WI 54906
Phone: +1.877.289.1235
International: +1.920.232.3275

STORAGE AND HANDLING

Tamper resistant for your protection. Use only if safety seal is intact